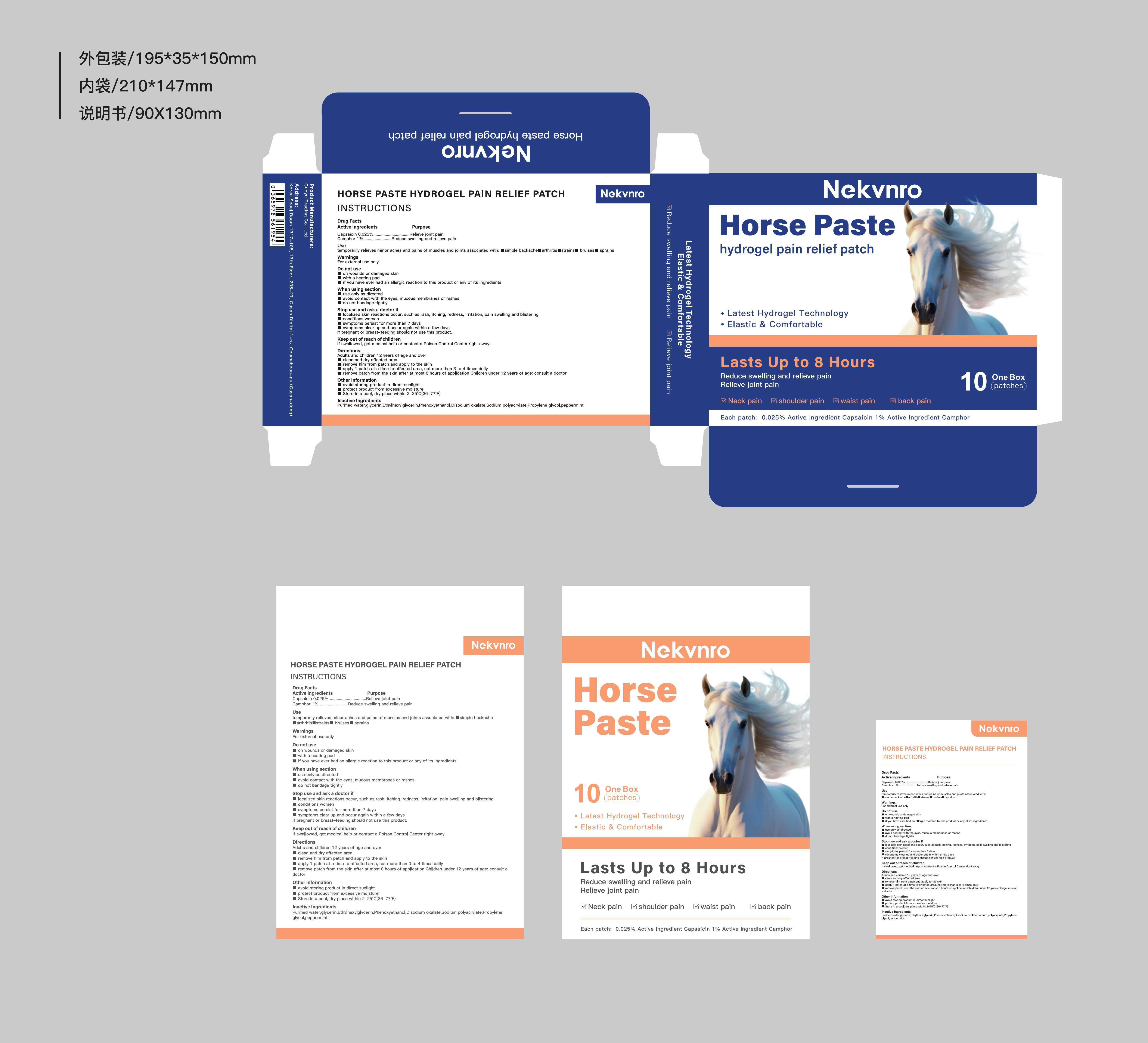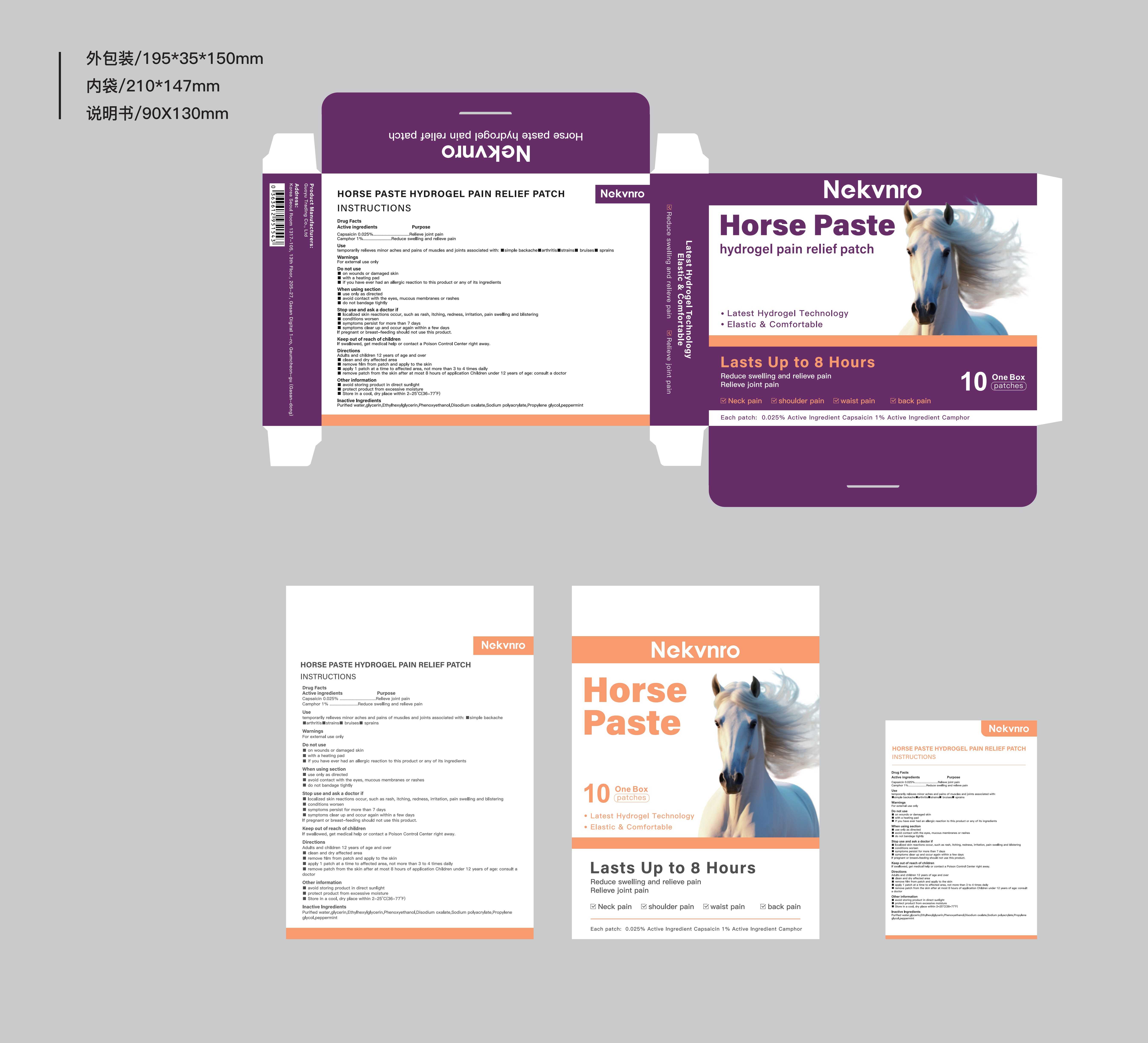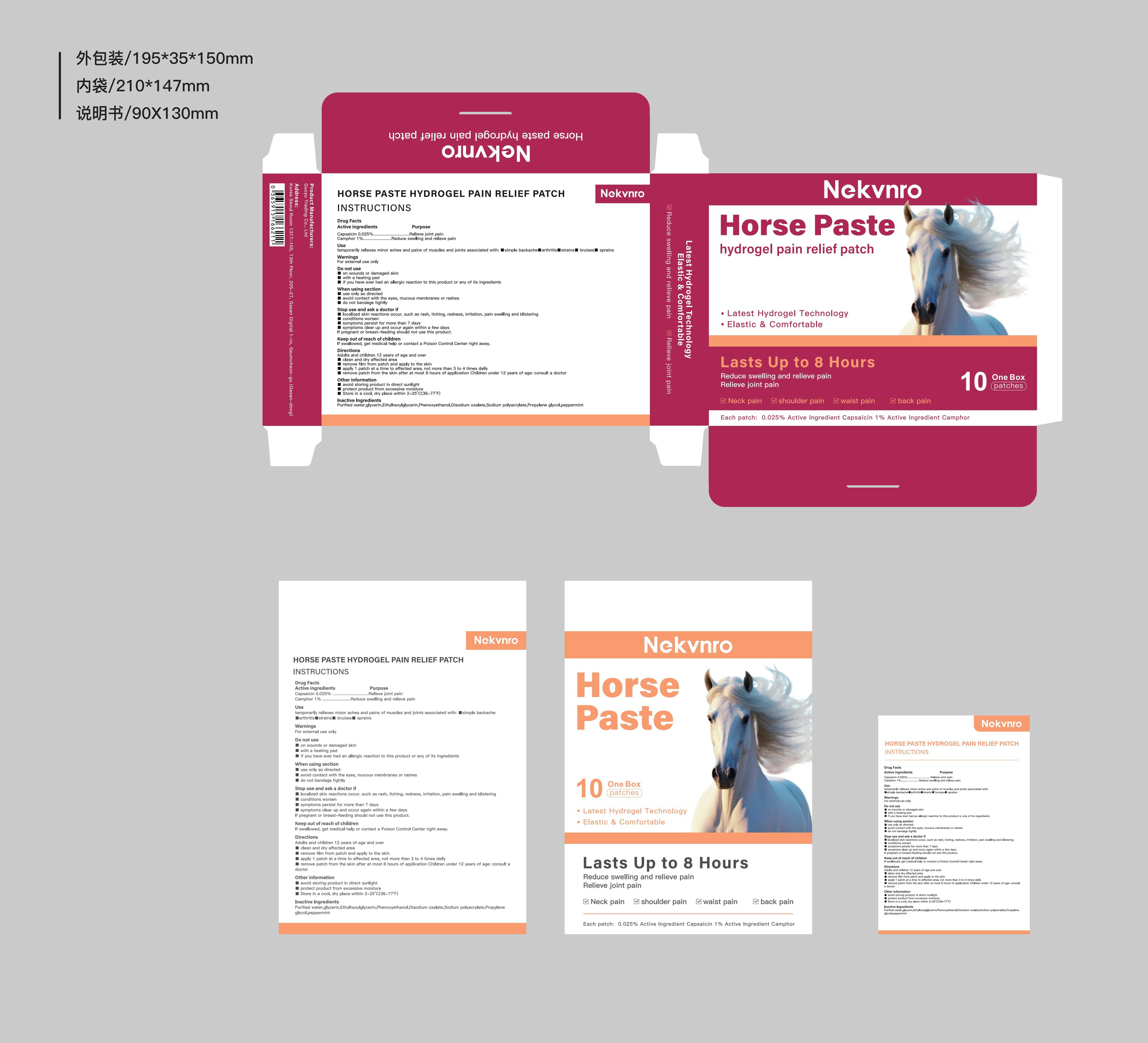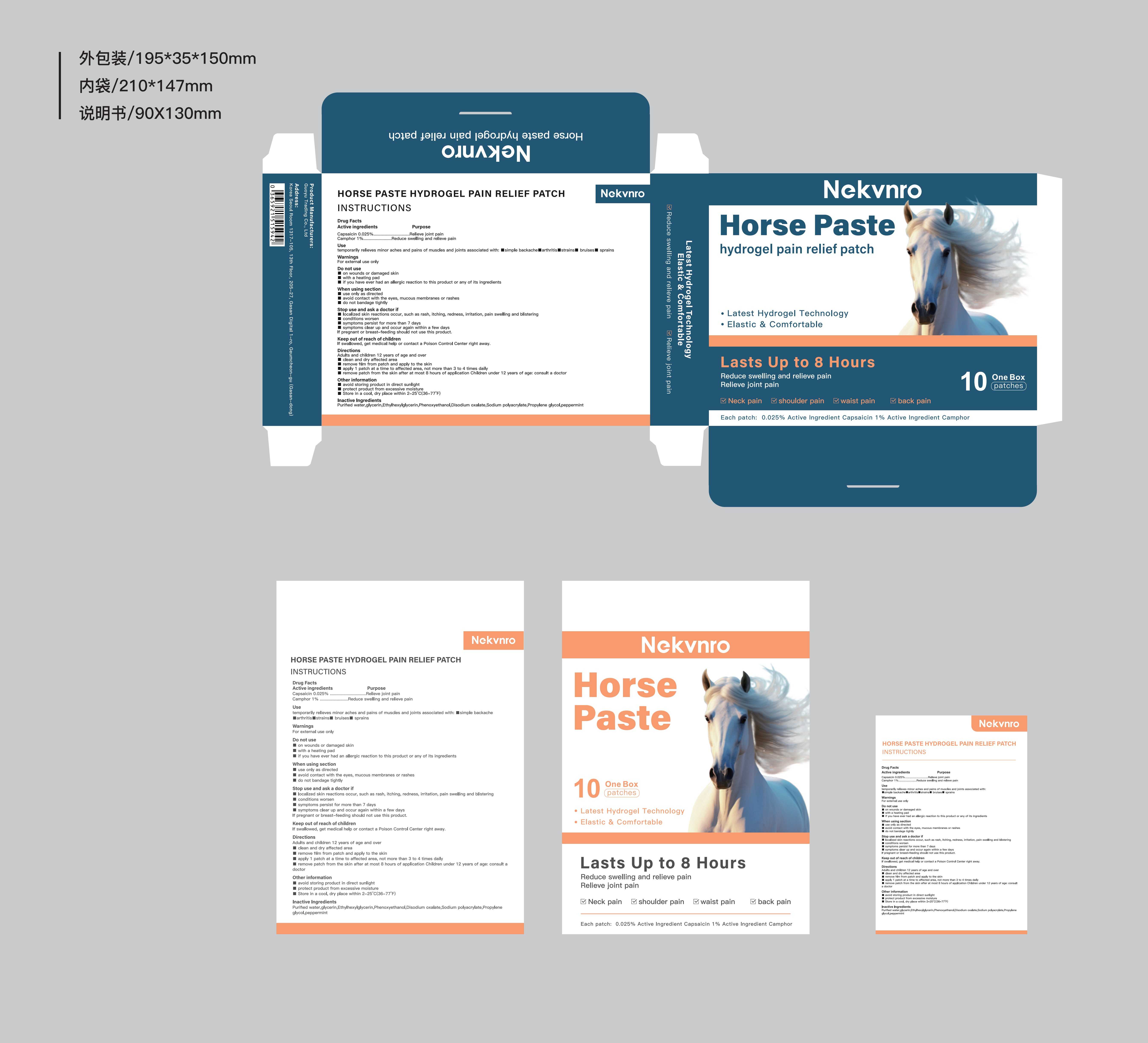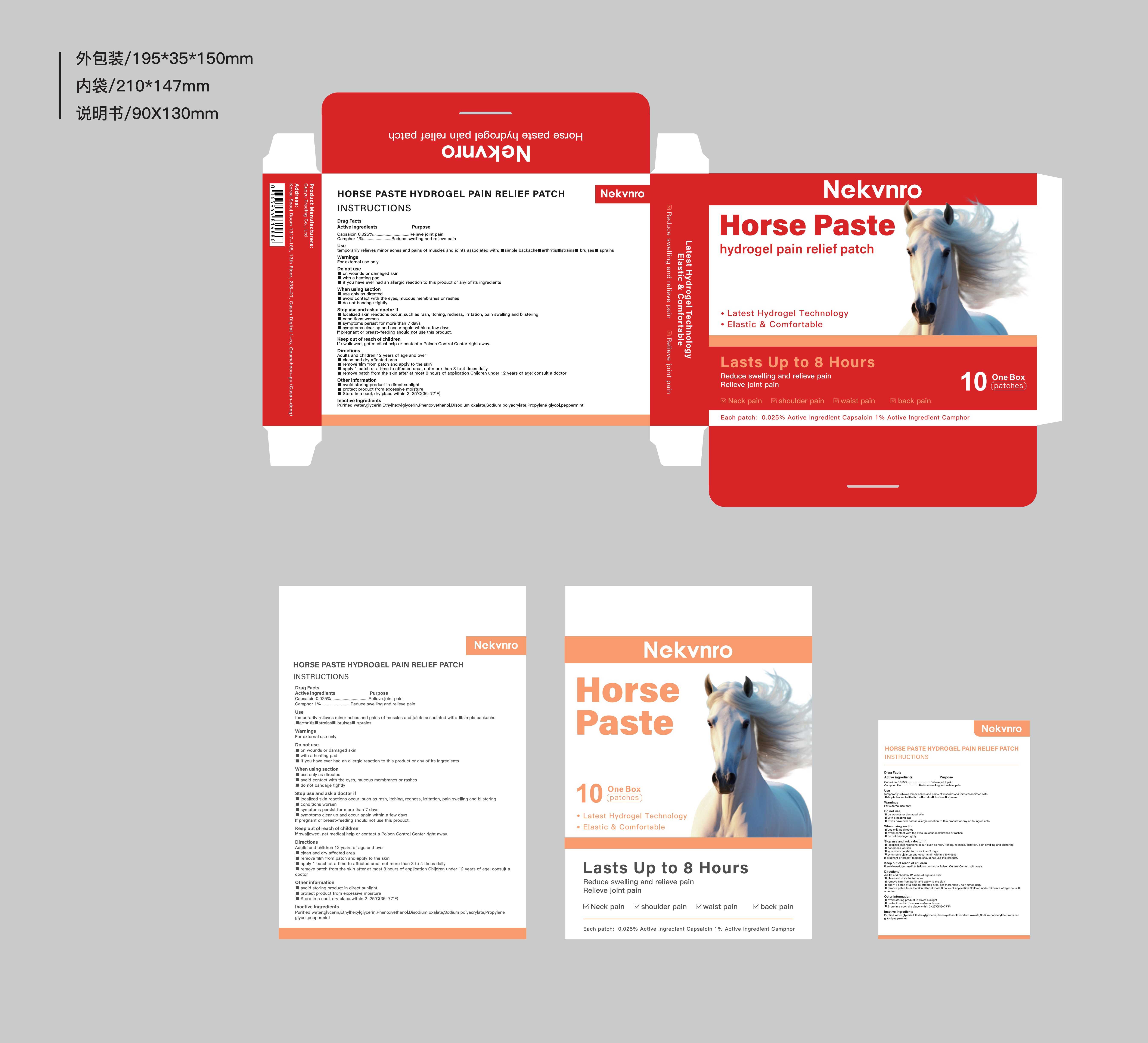 DRUG LABEL: Nekvnro Horse Paste. Hydrogel Pain Relief Patch
NDC: 84844-011 | Form: PATCH
Manufacturer: Guoyu Trading Co., Ltd.
Category: otc | Type: HUMAN OTC DRUG LABEL
Date: 20241105

ACTIVE INGREDIENTS: CAPSAICIN 0.025 g/100 1; CAMPHORIC ACID, (-)- 1 g/100 1
INACTIVE INGREDIENTS: PHENOXYETHANOL; WATER; PROPYLENE GLYCOL; ETHYLHEXYLGLYCERIN; DISODIUM OXALOACETATE; PEPPERMINT; GLYCERIN; SODIUM POLYACRYLATE (2500000 MW)

84844-011

Active Ingredient

Capsaicin 0.025%
Camphor 1%

Purpose

Relieve joint pain
Reduce swelling and relieve pain

Use

temporarily relieves minor aches and pains of muscles and joints associated with:

■simple backache

■arthritis

■strains

■ bruises

■ sprains

Warnings

For external use only

Do not use

■ on wounds or damaged skin
■ with a heating pad
■ if you have ever had an allergic reaction to this product or any of its ingredients

When Using

■ use only as directed
■ avoid contact with the eyes, mucous membranes or rashes
■ do not bandage tightly

Stop Use

■ localized skin reactions occur, such as rash, itching, redness, irritation, pain swelling and blistering
■ conditions worsen
■ symptoms persist for more than 7 days
■ symptoms clear up and occur again within a few days
If pregnant or breast-feeding should not use this product.

Ask Doctor

■ localized skin reactions occur, such as rash, itching, redness, irritation, pain swelling and blistering
■ conditions worsen
■ symptoms persist for more than 7 days
■ symptoms clear up and occur again within a few days
If pregnant or breast-feeding should not use this product.

Keep Oot Of Reach Of Children

Keep out of reach of children
If swallowed, get medical help or contact a Poison Control Center right away.

Directions

Adults and children 12 years of age and over
■ clean and dry affected area
■ remove film from patch and apply to the skin
■ apply 1 patch at a time to affected area, not more than 3 to 4 times daily
■ remove patch from the skin after at most 8 hours of application Children under 12 years of age: consult a doctor

Other information

■ avoid storing product in direct sunlight
■ protect product from excessive moisture
■ Store in a cool, dry place within 2-25°C(36-77°F)

Inactive ingredients

Purified water,glycerin,Ethylhexylglycerin,Phenoxyethanol,Disodium oxalate,Sodium polyacrylate,Propylene glycol,peppermint